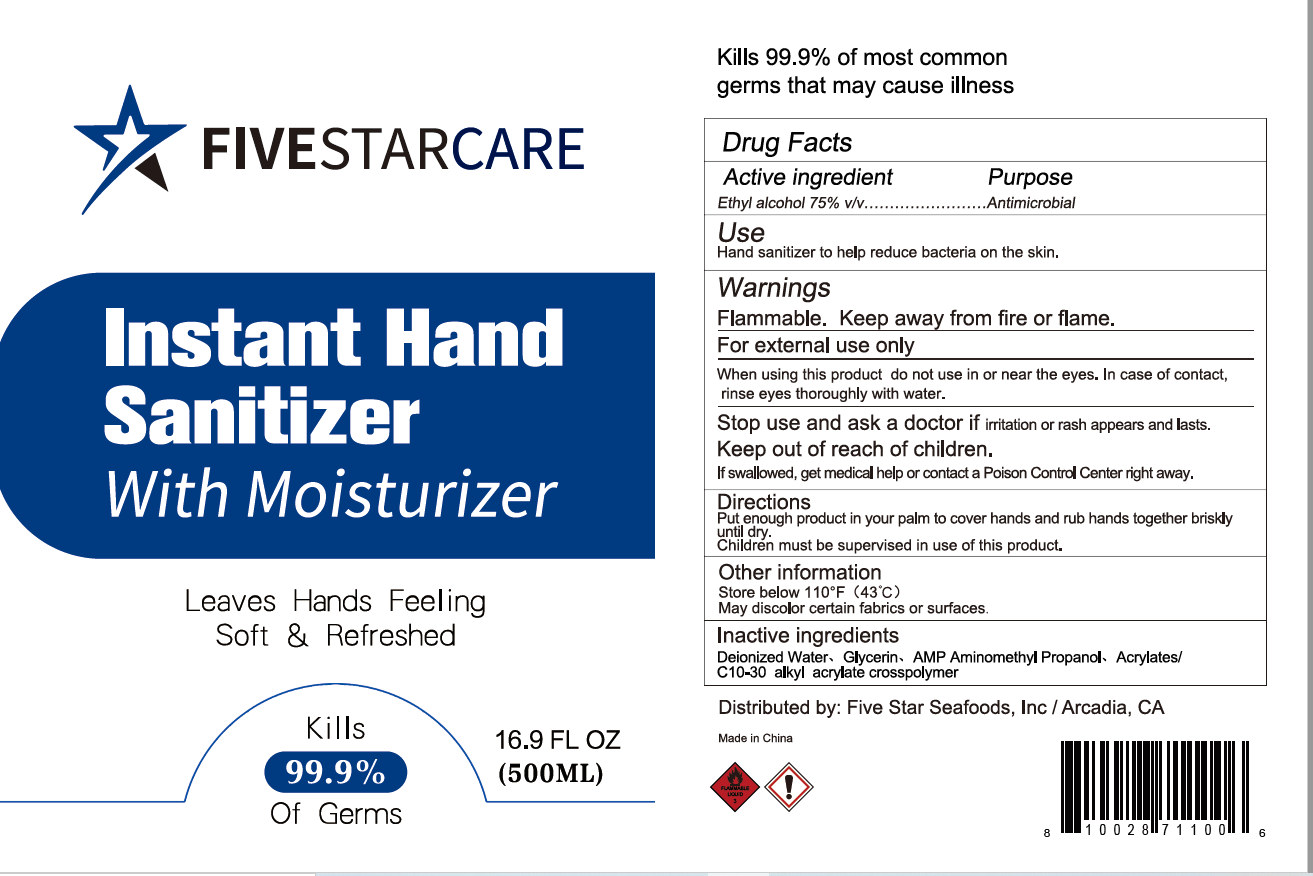 DRUG LABEL: Hand sanitizer
NDC: 55453-004 | Form: GEL
Manufacturer: Guangzhou Yikang Biotechnology Co., Ltd.
Category: otc | Type: HUMAN OTC DRUG LABEL
Date: 20200618

ACTIVE INGREDIENTS: ALCOHOL 375 mL/500 mL
INACTIVE INGREDIENTS: GLYCERIN; CARBOMER INTERPOLYMER TYPE A (55000 CPS); WATER; AMINOMETHYLPROPANOL

DOSAGE AND ADMINISTRATION

Store below 110°F (43°C)

INACTIVE INGREDIENT

AQUA, Glycerin, ACRYLATES/C10-30 ALKYL ACRYLATE CROSSPOLYMER、AMP AMINOMETHYL PROPANOL

INDICATIONS AND USAGE

Put enough product in your palm to cover hands and rub hands together briskly until dry.

ACTIVE INGREDIENT

ALCOHOL

keep out of reach of children

PURPOSE

Disinfection
Sterilization
No Rinseing

WARNINGS

Flammable. Keep away from fire or flame.For external use only。When using this product do not use in or near the eyes. In case of contact,rinse eyes thoroughly with water.Stop use and ask a doctor if iritation or rash appears and lasts.Keep out of reach of children.
If swallwed, get medical help or contact a Poison Control Center right away.